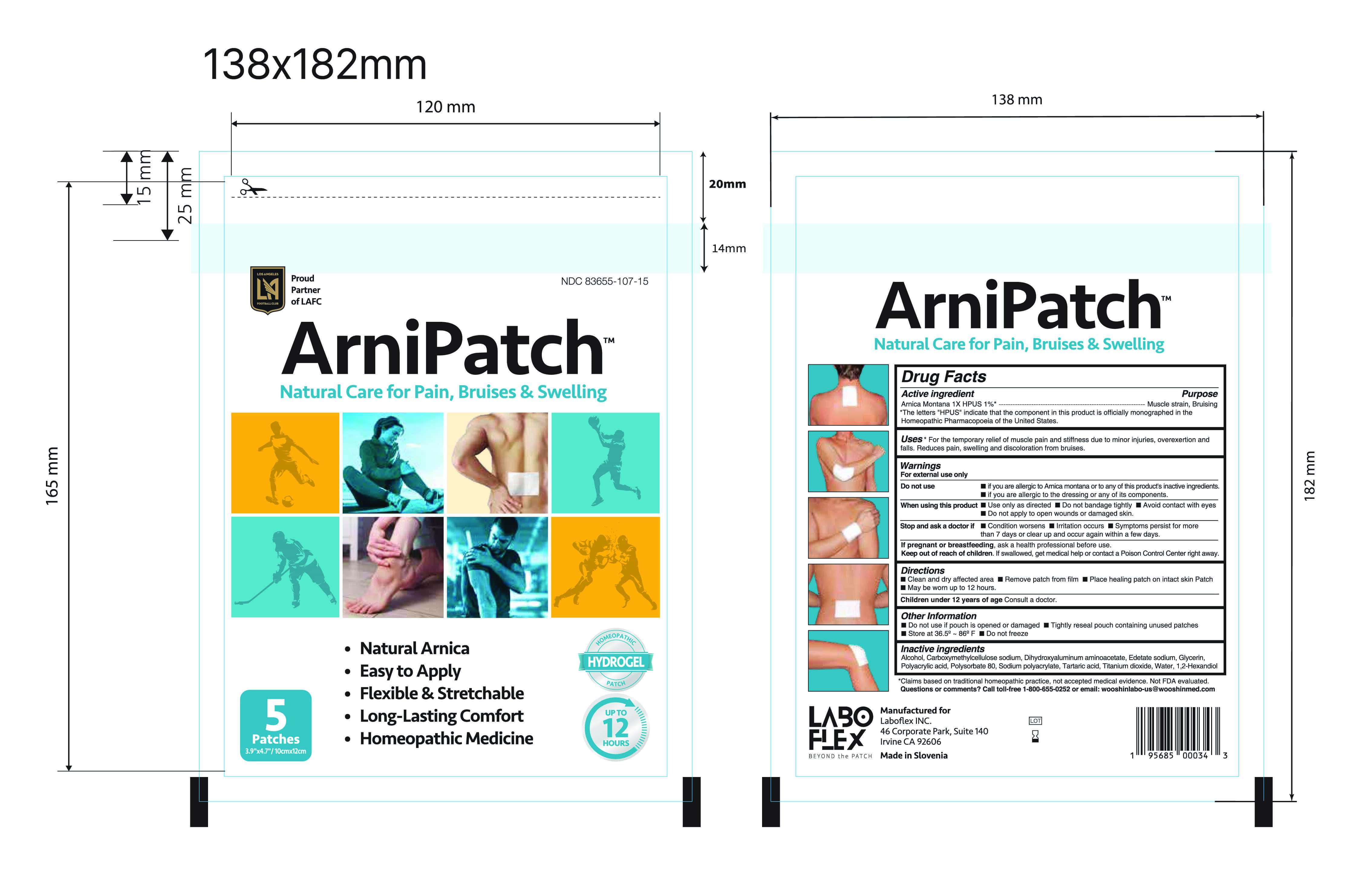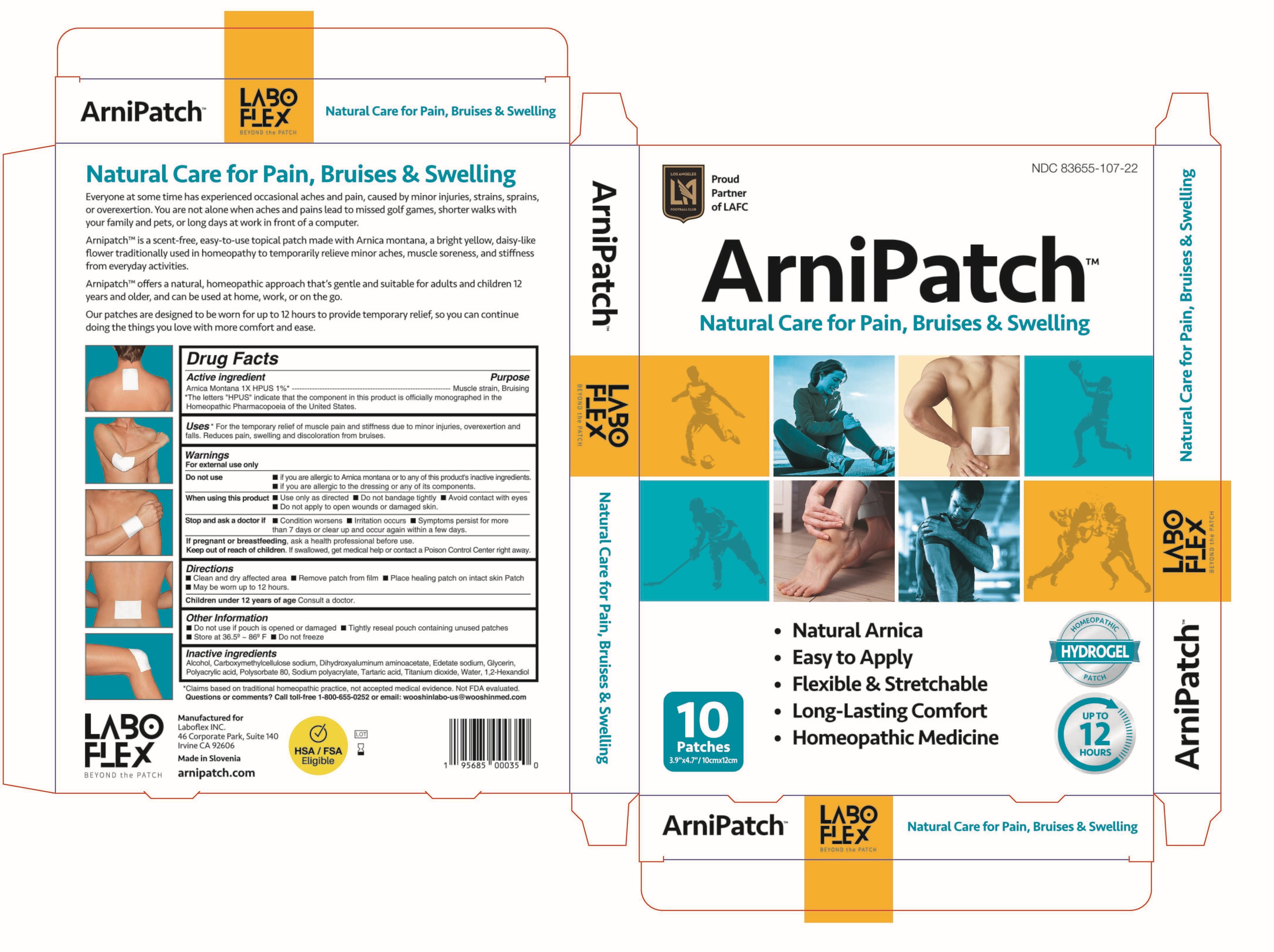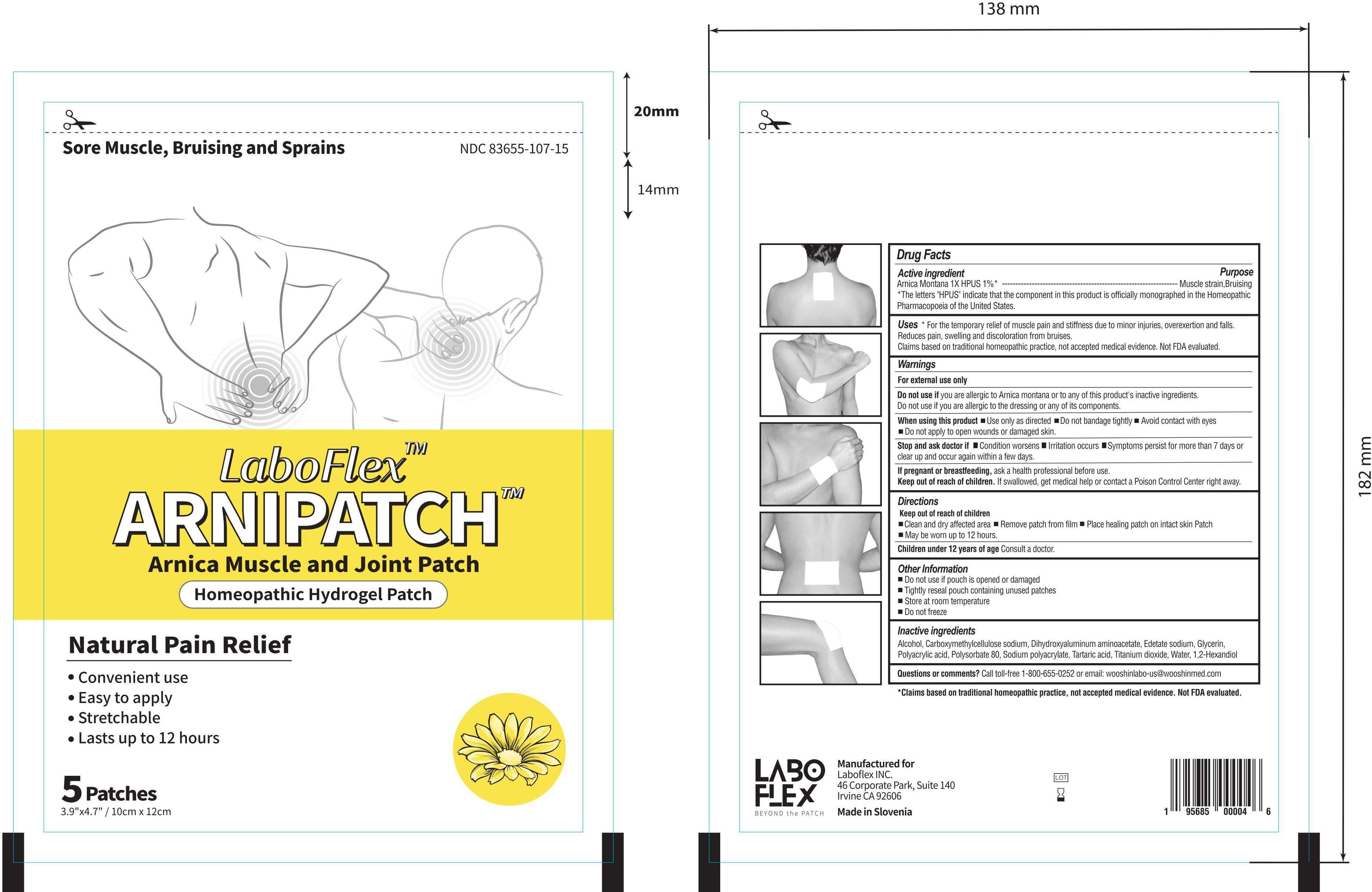 DRUG LABEL: LABOFLEX Arnipatch Muscle and Joint Patch
NDC: 83655-107 | Form: PATCH
Manufacturer: Laboflex, Inc.
Category: homeopathic | Type: HUMAN OTC DRUG LABEL
Date: 20250519

ACTIVE INGREDIENTS: ARNICA MONTANA 1 [hp_X]/1 g
INACTIVE INGREDIENTS: GLYCERIN; CARBOXYMETHYLCELLULOSE SODIUM, UNSPECIFIED FORM; DIHYDROXYALUMINUM AMINOACETATE; TITANIUM DIOXIDE; POLYACRYLIC ACID (8000 MW); POLYSORBATE 80; SODIUM POLYACRYLATE (8000 MW); WATER; TARTARIC ACID; ALCOHOL; 1,2-HEXANEDIOL; EDETATE SODIUM

LABOFLEX Arnipatch Arnica Muscle and Joint Patch

Active Ingredients

Arnica Montana 1X - 1% HPUS

Purpose

Muscle strain, Bruising

Uses

- * For the temporary relief of muscle pain and stiffness due to minor injuries, overexertion and
  falls. Reduces pain, swelling and discoloration from bruises.

Warnings

For external use only.

Do not useif you are allergic to Arnica montana or to any of this product's inactive ingredients. Do not use if you are allergic to the dressing or any of its components.

When using this product■ Use only as directed ■ Do not bandage tightly ■ Avoid contact with eyes ■ Do not apply to open wounds or damaged skin

Keep out of reach of children. If swallowed, get medical help or contact a Posion Control Center right away.

Stop and ask doctor if■Condition worsens ■ Irritation occurs ■ Symptoms persist for more than 7 days or clear up and occur again within a few days

If pregnant or breastfeeding, ask a health professional before use.

Directions

Keep out of reach of children

■ Clean and dry affected area ■ Remove patch from film ■ Place healing patch on intact skin ■ Patch may be worn up to 12 hours.

Children under 12 years of age Consult a doctor

Inactive Ingredients

Alcohol, Carboxymethylcellulose Sodium, Dihydroxyaluminum Aminoacetate, Edetate Sodium, Glycerin, Polyacrylic Acid, Polysorbate 80, Sodium Polyacrylate, Tartaric Acid, Titanium Dioxide, 1,2-Hexandiol, Purified Water

Questions of comments?

Call toll-free 1-800-655-0252 or email: wooshinlabo-us@wooshinmed.com